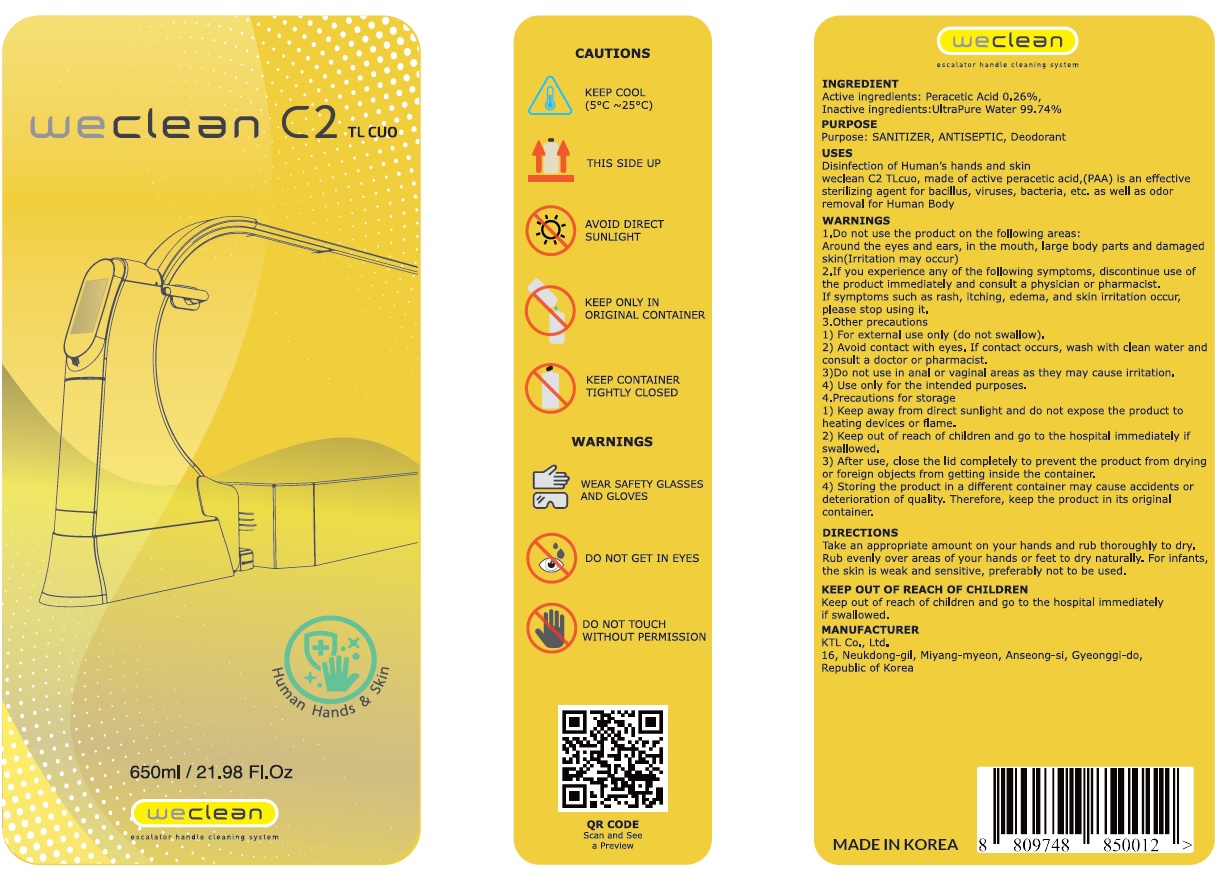 DRUG LABEL: WECLEAN C2 TLCUO
NDC: 74438-070 | Form: LIQUID
Manufacturer: KTL LTD
Category: otc | Type: HUMAN OTC DRUG LABEL
Date: 20201029

ACTIVE INGREDIENTS: PERACETIC ACID 0.26 g/100 mL
INACTIVE INGREDIENTS: Water

ACTIVE INGREDIENT

Peroxy acetic acid 0.26%

INACTIVE INGREDIENT

Water

PURPOSE

SANITIZER, ANTISEPTIC, Deodorant

WARNINGS

1.Do not use the product on the following areas:

Around the eyes and ears, in the mouth, large body parts and damaged skin(Irritation may occur)

2.If you experience any of the following symptoms, discontinue use of the product immediately and consult a physician or pharmacist.

If symptoms such as rash, itching, edema, and skin irritation occur, please stop using it.
3.Other precautions
1) For external use only (do not swallow).

2) Avoid contact with eyes. If contact occurs, wash with clean water and consult a doctor or pharmacist.

3)Do not use in anal or vaginal areas as they may cause irritation.

4) Use only for the intended purposes.

4.Precautions for storage
1) Keep away from direct sunlight and do not expose the product to heating devices or flame.

2) Keep out of reach of children and go to the hospital immediately if swallowed.

3) After use, close the lid completely to prevent the product from drying or foreign objects from getting inside the container.

4) Storing the product in a different container may cause accidents or deterioration of quality. Therefore, keep the product in its original container.

Keep out of reach of children and go to the hospital immediately if swallowed.

Uses

Disinfection of Human’s hands and skin weclean C2 TLcuo, made of active peracetic acid,(PAA) is an effective sterilizing agent for bacillus, viruses, bacteria, etc. as well as odor removal for Human Body

Directions

Take an appropriate amount on your hands and rub thoroughly to dry.
Rub evenly over areas of your hands or feet to dry naturally. For infants, the skin is weak and sensitive, preferably not to be used.